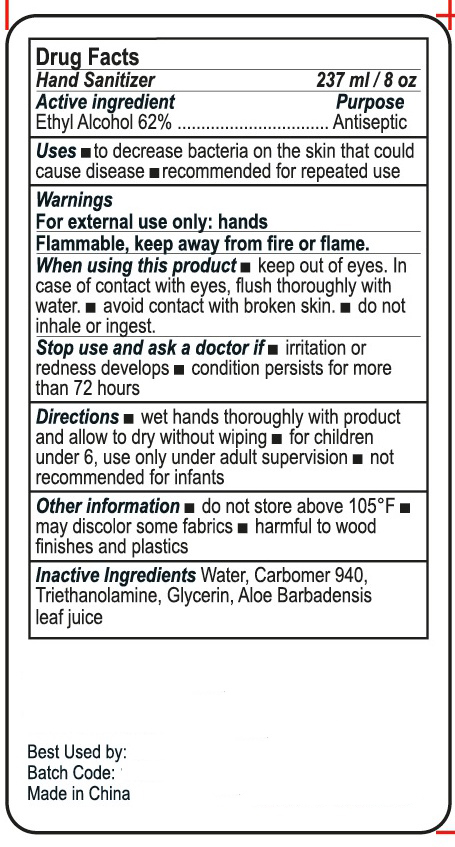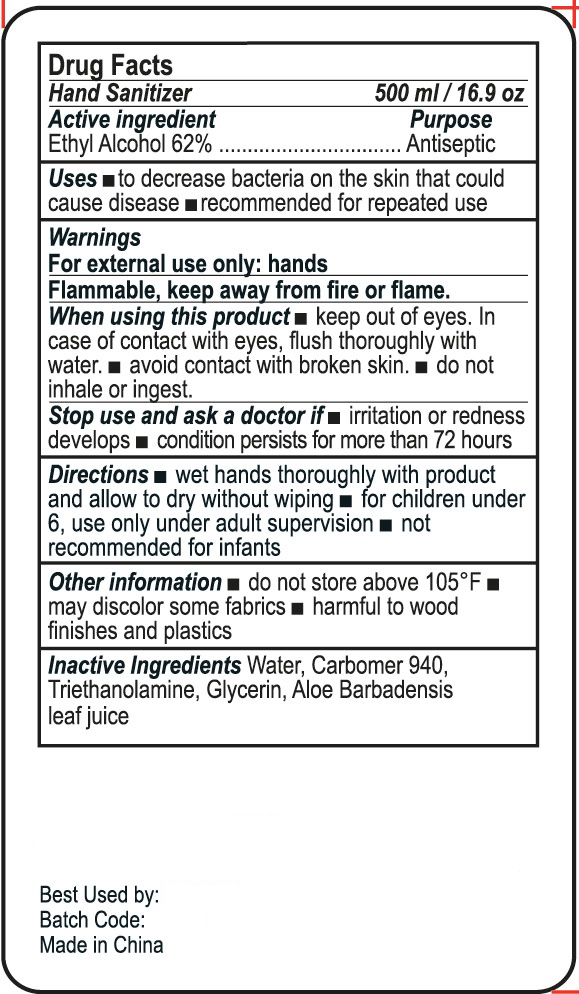 DRUG LABEL: HAND SANITIZER
NDC: 47993-258 | Form: GEL
Manufacturer: NINGBO JIANGBEI OCEAN STAR TRADING CO.,LTD
Category: otc | Type: HUMAN OTC DRUG LABEL
Date: 20201104

ACTIVE INGREDIENTS: ALCOHOL 62 g/112 mL
INACTIVE INGREDIENTS: CARBOMER 940; ALOE VERA LEAF; WATER; GLYCERIN; TRIETHANOLAMINE BENZOATE

47993-258

Active ingredients

Ethyl Alcohol 62%

PURPOSE

Antiseptic

Uses：

- To decrease bacteria on the skin that could cause disease.
- Recommended for repeated use.

Warnings:

For external use only：hands

Flammable，keep away from fire or flame.

When using this product.

- Keep out of eyes. In case of contact with eyes，flush thoroughly with water.
- Avoid contact with broken skin.
- Do not inhale or ingest.

Stop use and ask a doctor if

- Irritation or redness develops.
- Condition persists for more than 72 hours.

Directions:

- Wet hands thoroughly with product and allow to dry without wiping.
- For children under 6，use only under adult supervision.
- Not recommended for infants.

KEEP OUT OF REACH OF CHILDREN

For children under 6，use only under adult supervision.

Other information

- Do not store above 105 ℉
- May discolor some fabrics
- Harmful to wood finishes and plastics

Inactive Ingredients:

Water,Carbomer 940,Triethanolamine,Glycerin,Aloe Barbadensis leaf juice